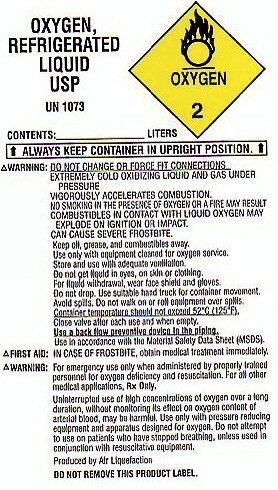 DRUG LABEL: OXYGEN
NDC: 42887-001 | Form: GAS
Manufacturer: North Central Respiratory, Inc
Category: prescription | Type: HUMAN PRESCRIPTION DRUG LABEL
Date: 20251105

ACTIVE INGREDIENTS: OXYGEN 99 L/100 L

PRODUCT WARNINGS AND PRECAUTIONS

OXYGEN REFRIGERATED LIQUID USP UN 1073 OXYGEN-2

CONTENTS________________ LITERS ALWAYS KEEP CONTAINER IN UPRIGHT POSITION.

WARNING: DO NOT CHANGE OR FORCE FIT CONNECTIONS. EXTREMELY COLD OXIDIZING LIQUID AND GAS UNDER PRESSURE. VIGOROUSLY ACCELERATES COMBUSTION. NO SMOKING IN THE PRESENCE OF OXYGEN OR A FIRE MAY RESULT. COMBUSTIBLES IN CONTACT WITH LIQUID OXYGEN MAY EXPLODE ON IGNITION OR IMPACT. CAN CAUSE SEVERE FROSTBITE.

KEEP OIL GREASE AND COMBUSTIBLES AWAY. USE ONLY WITH EQUIPMENT CLEANED FOR OXYGEN SERVICE. STORE AND USE WITH ADEQUATE VENTILATION. DO NOT GET LIQUID IN EYES, ON SKIN OR CLOTHING. FOR LIQUID WITHDRAWAL WEAR FACE SHIELD AND GLOVES DO NOT DROP. USE SUITABLE HAND TRUCK FOR CONTAINER MOVEMENT. AVOID SPILLS. DO NOT WALK ON OR ROLL EQUIPMENT OVER SPILLS. CONTAINER TEMPERATURE SHOULD NOT EXCEED 52 C (125 F). CLOSE VALVE AFTER EACH USE AND WHEN EMPTY. USE A BACK FLOW PREVENTATIVE DEVICE IN THE PIPING. USE IN ACCORDANCE WITH THE MATERIAL SAFETY DATA SHEET (MSDS).

CAS NO 7782-44-7

OXYGEN REFRIGERATED LIQUID LABEL

OXYGEN REFRIGERATED LIQUID USP UN 1073 OXYGEN-2

CONTENTS________________ LITERS ALWAYS KEEP CONTAINER IN UPRIGHT POSITION.

WARNING: DO NOT CHANGE OR FORCE FIT CONNECTIONS. EXTREMELY COLD OXIDIZING LIQUID AND GAS UNDER PRESSURE. VIGOROUSLY ACCELERATES COMBUSTION. NO SMOKING IN THE PRESENCE OF OXYGEN OR A FIRE MAY RESULT. COMBUSTIBLES IN CONTACT WITH LIQUID OXYGEN MAY EXPLODE ON IGNITION OR IMPACT. CAN CAUSE SEVERE FROSTBITE.

KEEP OIL GREASE AND COMBUSTIBLES AWAY. USE ONLY WITH EQUIPMENT CLEANED FOR OXYGEN SERVICE. STORE AND USE WITH ADEQUATE VENTILATION. DO NOT GET LIQUID IN EYES, ON SKIN OR CLOTHING. FOR LIQUID WITHDRAWAL WEAR FACE SHIELD AND GLOVES DO NOT DROP. USE SUITABLE HAND TRUCK FOR CONTAINER MOVEMENT. AVOID SPILLS. DO NOT WALK ON OR ROLL EQUIPMENT OVER SPILLS. CONTAINER TEMPERATURE SHOULD NOT EXCEED 52 C (125 F). CLOSE VALVE AFTER EACH USE AND WHEN EMPTY. USE A BACK FLOW PREVENTATIVE DEVICE IN THE PIPING. USE IN ACCORDANCE WITH THE MATERIAL SAFETY DATA SHEET (MSDS).

CAS NO 7782-44-7

res